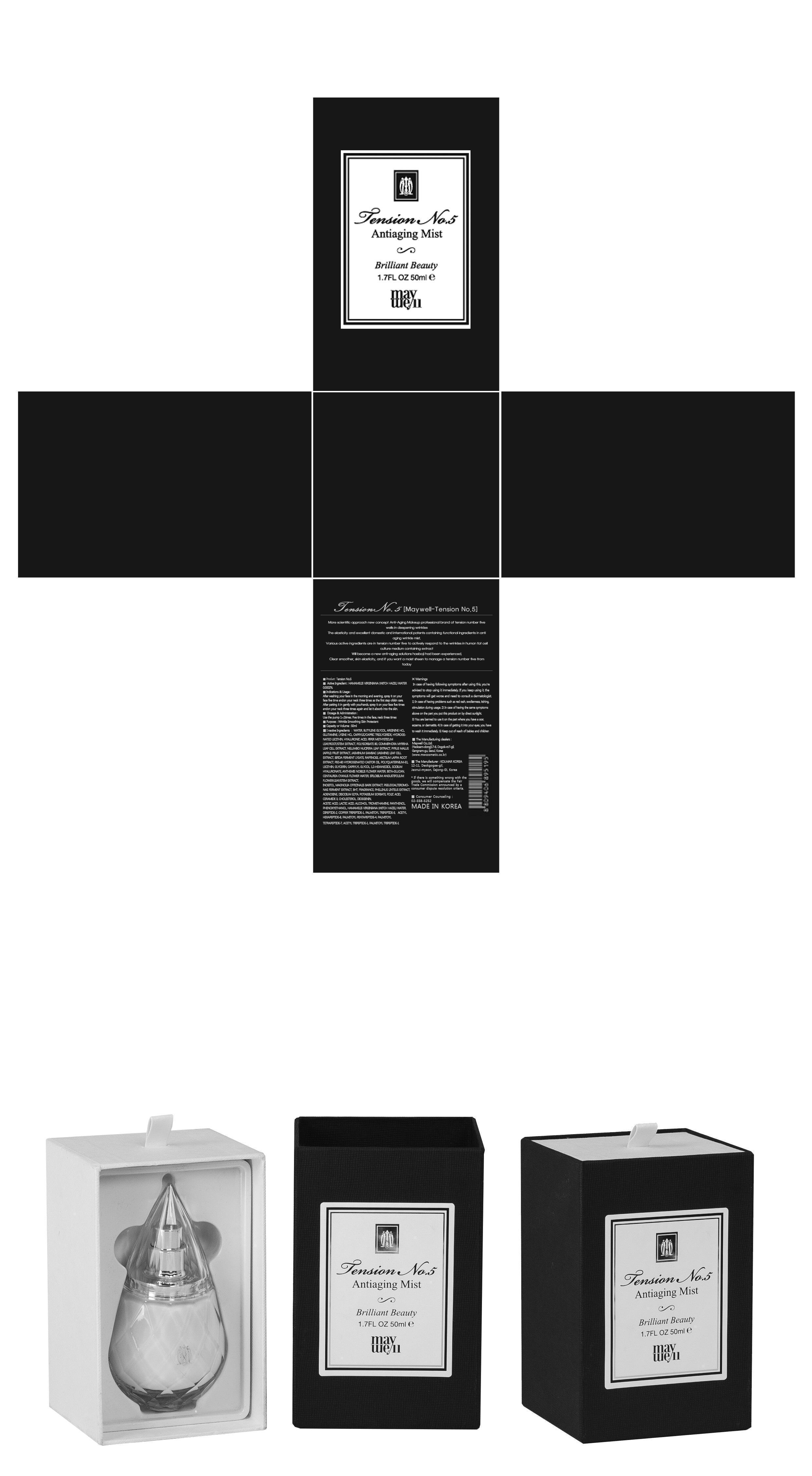 DRUG LABEL: TENSION NO. 5
NDC: 69628-010 | Form: CREAM
Manufacturer: Maywell Co., Ltd.
Category: otc | Type: HUMAN OTC DRUG LABEL
Date: 20191220

ACTIVE INGREDIENTS: WITCH HAZEL 0.0001 mg/50 mL
INACTIVE INGREDIENTS: WATER; BUTYLENE GLYCOL

ACTIVE INGREDIENT

Active Ingredient: HAMAMELIS VIRGINIANA (WITCH HAZEL) WATER 0.0002%

INACTIVE INGREDIENT

Inactive Ingredients: WATER, BUTYLENE GLYCOL, ARGININE HCL, GLUTAMINE, LYSINE HCL, CAPRYLIC/CAPRIC TRIGLYCERIDE, HYDROGENATED LECITHIN, HYALURONIC ACID, PIPER METHYSTICUM LEAF/ROOT/STEM EXTRACT, POLYSORBATE 80, COMMIPHORA MYRRHA LEAF CELL EXTRACT, NELUMBO NUCIFERA LEAF EXTRACT, PYRUS MALUS (APPLE) FRUIT EXTRACT, JASMINUM SAMBAC (JASMINE) LEAF CELL EXTRACT, BIFIDA FERMENT LYSATE, RAFFINOSE, ARCTIUM LAPPA ROOT EXTRACT, PEG-60 HYDROGENATED CASTOR OIL, POLYQUATERNIUM-51, LECITHIN, GLYCERIN, CAPRYLYL GLYCOL, 1,2-HEXANEDIOL, SODIUM HYALURONATE, ANTHEMIS NOBILIS FLOWER WATER, BETA-GLUCAN, CENTAUREA CYANUS FLOWER WATER, EPILOBIUM ANGUSTIFOLIUM FLOWER/LEAF/STEM EXTRACT, INOSITOL, MAGNOLIA OFFICINALIS BARK EXTRACT, PSEUDOALTEROMONAS FERMENT EXTRACT, BHT, FRAGRANCE, PHELLINUS LINTEUS EXTRACT, ADENOSINE, DISODIUM EDTA, POTASSIUM SORBATE, FOLIC ACID, CERAMIDE 3, CHOLESTEROL, DIOSGENIN, ACETIC ACID, LACTIC ACID, ALCOHOL, TROMETHAMINE, PANTHENOL, PHENOXYETHANOL, DIPEPTIDE-2, COPPER TRIPEPTIDE-1, PALMITOYL TRIPEPTIDE-5, ACETYL HEXAPEPTIDE-8, PALMITOYL PENTAPEPTIDE-4, PALMITOYL TETRAPEPTIDE-7, ACETYL TRIPEPTIDE-1, PALMITOYL TRIPEPTIDE-1

PURPOSE

Purpose: Skin Protectant

WARNINGS

Warnings: 1. In case of having following symptoms after using this, you’re advised to stop using it immediately. If you keep using it, the symptoms will get worse and need to consult a dermatologist. 1) In case of having problems such as red rash, swollenness, itching, stimulation during usage. 2) In case of having the same symptoms above on the part you put this product on by direct sunlight. 2. You are banned to use it on the part where you have a scar, eczema, or dermatitis. 3. In case of getting it into your eyes, you have to wash it immediately.

KEEP OUT OF REACH OF CHILDREN

Keep out of reach of babies and children

INDICATIONS & USAGE

Indications & Usage: After washing your face in the morning and evening, spray it on your face five time and on your neck three times as the first step of skin care. After patting it in gently with your hands, spray it on your face five times and on your neck three times again and let it absorb into the skin.

DOSAGE & ADMINISTRATION

Dosage & Administration: Five times in the face, neck three times